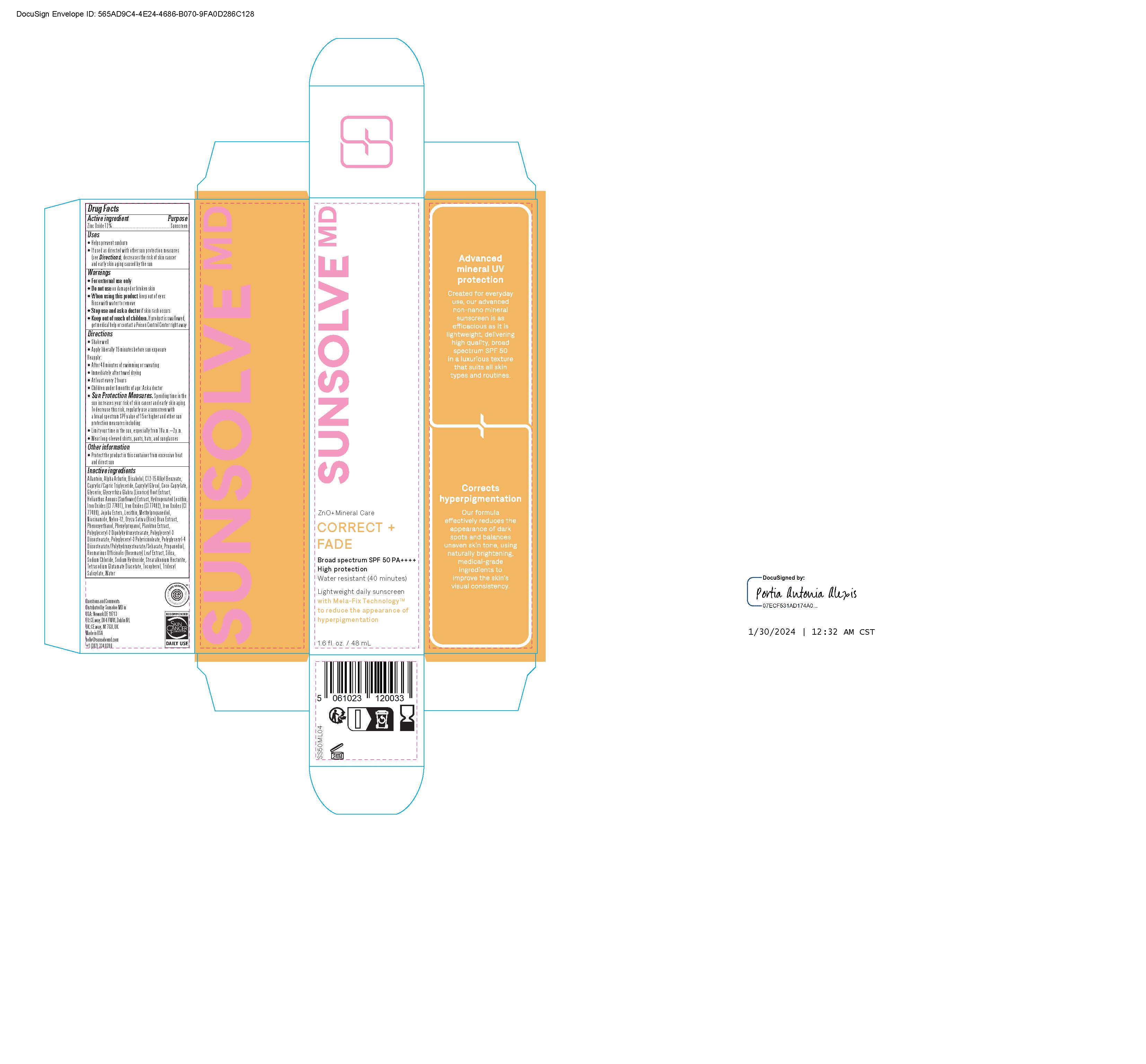 DRUG LABEL: Sunsolve MD Correct and Fade
NDC: 84878-200 | Form: LOTION
Manufacturer: Sunsolve MD Inc
Category: otc | Type: HUMAN OTC DRUG LABEL
Date: 20251114

ACTIVE INGREDIENTS: ZINC OXIDE 132 mg/1 mL
INACTIVE INGREDIENTS: STEARALKONIUM HECTORITE; POLYGLYCERYL-3 DIISOSTEARATE; POLYGLYCERYL-4 DIISOSTEARATE/POLYHYDROXYSTEARATE/SEBACATE; FERROSOFERRIC OXIDE; FERRIC OXIDE YELLOW; PHENOXYETHANOL; CAPRYLIC/CAPRIC TRIGLYCERIDE; FERRIC OXIDE RED; GLYCERIN; TOCOPHEROL; GLYCYRRHIZA GLABRA (LICORICE) ROOT; JOJOBA OIL; ORYZA SATIVA WHOLE; TRIDECYL SALICYLATE; SILICON DIOXIDE; CAPRYLYL GLYCOL; COCO-CAPRYLATE; NYLON-12; PHENYLPROPANOL; HELIANTHUS ANNUUS FLOWERING TOP; LECITHIN, SOYBEAN; METHYLPROPANEDIOL; POLYGLYCERYL-2 DIPOLYHYDROXYSTEARATE; ALLANTOIN; ALKYL (C12-15) BENZOATE; ROSMARINUS OFFICINALIS FLOWER; .ALPHA.-BISABOLOL, (+)-; SODIUM HYDROXIDE; WATER; NIACINAMIDE; PROPANEDIOL; TETRASODIUM GLUTAMATE DIACETATE; SODIUM CHLORIDE

Sunsolve MD Correct and Fade